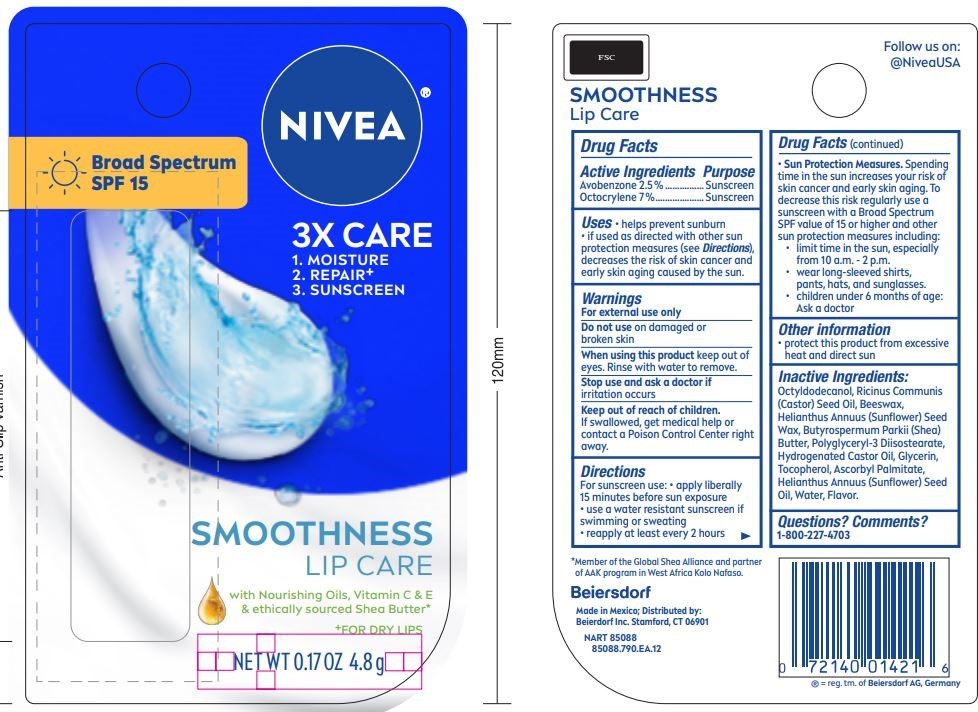 DRUG LABEL: Nivea Smoothness Lip Care
NDC: 10356-819 | Form: STICK
Manufacturer: Beiersdorf Inc
Category: otc | Type: HUMAN OTC DRUG LABEL
Date: 20251231

ACTIVE INGREDIENTS: AVOBENZONE 2.5 g/100 g; OCTOCRYLENE 7 g/100 g
INACTIVE INGREDIENTS: OCTYLDODECANOL; CASTOR OIL; GLYCERIN; YELLOW WAX; SHEA BUTTER; WATER; POLYGLYCERYL-3 DIISOSTEARATE; TOCOPHEROL; ASCORBYL PALMITATE; SUNFLOWER OIL; HYDROGENATED CASTOR OIL; HELIANTHUS ANNUUS SEED WAX

NIVEA Smoothness Lip Care

Active ingredients:

Avobenzone 2.5

Octocrylene 7%

Purpose:

Sunscreen

INDICATIONS AND USAGE

Uses • helps prevent sunburn • if used as directed with other sun protection measures (see Directions), decreases the risk of skin cancer and early skin aging caused by the sun

Warnings:

For external use only

Stop use and ask a doctor if rash occurs

Keep out of reach of children. If swallowed, get medical help or contact a
Poison Control Center right away

DOSAGE AND ADMINISTRATION

For sunscreen use

- apply liberally at least 15 minutes before sun exposure
- use a water resistant sunscreen if swimming or sweating
- reapply at least every two hours
- Sun Protection Measures. Spending time in the sun increases your risk of skin cancer and early skin aging. To decrease this risk regularly use a sunscreen with a Broad SpectrumSPFvalue of 15 or higher and other sun protection measures including: •limit time in the sun, especially from 10 a.m. – 2 p.m. •wear long-sleeved shirts, pants, hats, and sunglasses
- children under 6 months of age: Ask a doctor

Inactive ingredients:

Octyldodecanol, Ricinus Communis (Castor) Seed Oil, Beeswax, Helianthus Annuus (Sunflower) Seed Wax, Butyrospermum Parkii (Shea) Butter, Polyglyceryl-3 Diisostearate, Hydrogenated Castor Oil, Glycerin, Tocopherol, Ascorbyl Palmitate, Helianthus Annuus (Sunflower) Seed Oil, Water, Flavor.

Questions? 1-800-227-4703

PACKAGE LABEL

NIVEA

Smoothness Lip Care

Broad spectrum SPF 15

3X Care:

1. MOISTURE 2. REPAIR+ 3. SUNSCREEN

with Nourishing Oils, Vitamin C & E & ethically sourced Shea Butter*

+FOR DRY LIPS